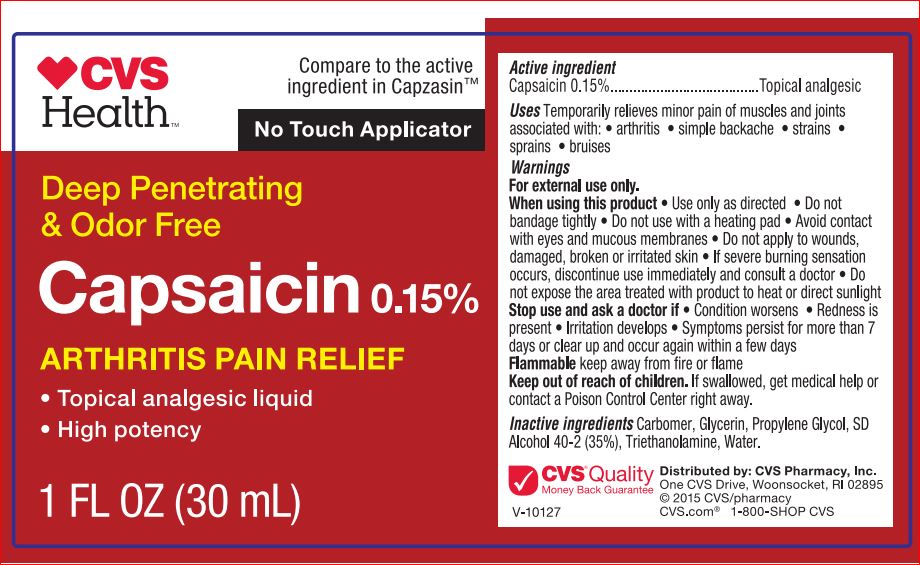 DRUG LABEL: Arthritis Pain Relief
NDC: 59779-237 | Form: LIQUID
Manufacturer: CVS
Category: otc | Type: HUMAN OTC DRUG LABEL
Date: 20171130

ACTIVE INGREDIENTS: CAPSAICIN .15 g/100 mL
INACTIVE INGREDIENTS: GLYCERIN; PROPYLENE GLYCOL; ALCOHOL; TROMETHAMINE; WATER

Active ingredient

Capsaicin 0.15%

Purpose

Topical analgesic

Uses

Temporarily relieves minor pain associated with:

- arthritis
- simple backache
- muscle strains
- muscle sprains
- bruises
- cramps

Warnings

For external use only

When using this product

- Use only as directed
- Do not bandage tightly
- Do not use with a heating pad
- Avoid contact with eyes and mucous membranes
- Do not apply to wounds, damaged, broken or irritated skin
- A transient burning sensation may occur upon application but generally disappears in several days
- If severe burning sensation occurs, discontinue use immediately and read packate insert for importan information
- Do not expose the area treated with product to hear or direct sunlight
- Avoid taking a bath or shower within 1 hour before or after applying

Stop use and ask a doctor if

- Condition worsens
- Redness is present
- Irritation develops
- Symptoms persist for more than 7 days or clear up and occur again within a few days

Flammable

keep away form fire or flame

If pregnant or breast-feeding,

ask a healthcare professional before use.

Keep out of reach of children.

If swallowed, get medical help or contact a Poison COntrol Center right away.

Directions

Adults and children over 18 years:

- Apply to affected area
- Massage into painful area until thoroughly absorbed
- Repeat as necessary, but no more than 3 to 4 times daily
- IF MEDICINE COMES IN CONTACT WITH HANDS, WASH WITH SOAP AND WATER

Children 18 years or younger: ask a doctor

Inactive ingredients

Carbomer, Glycerin, Propylene Glycol, SD Alcohol 40-2 (35%), Triethanolamine, Water.